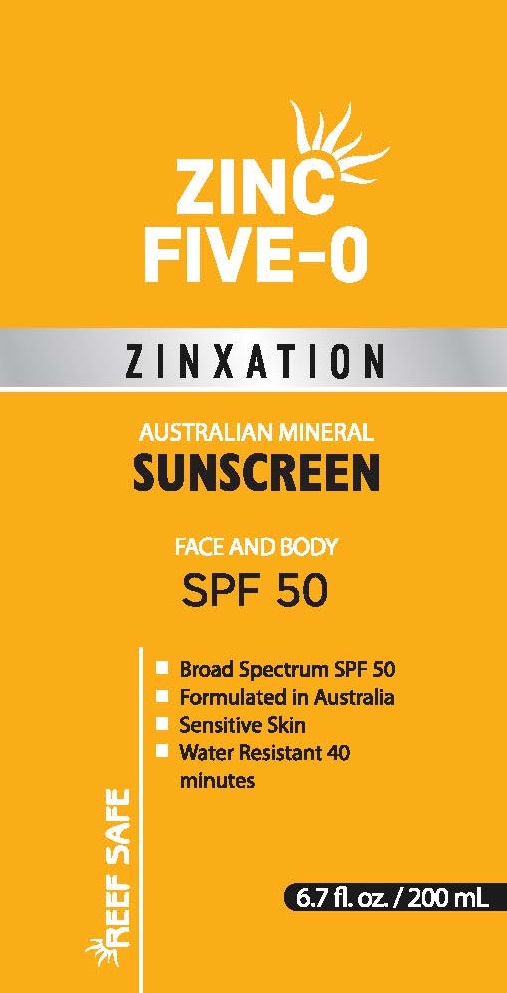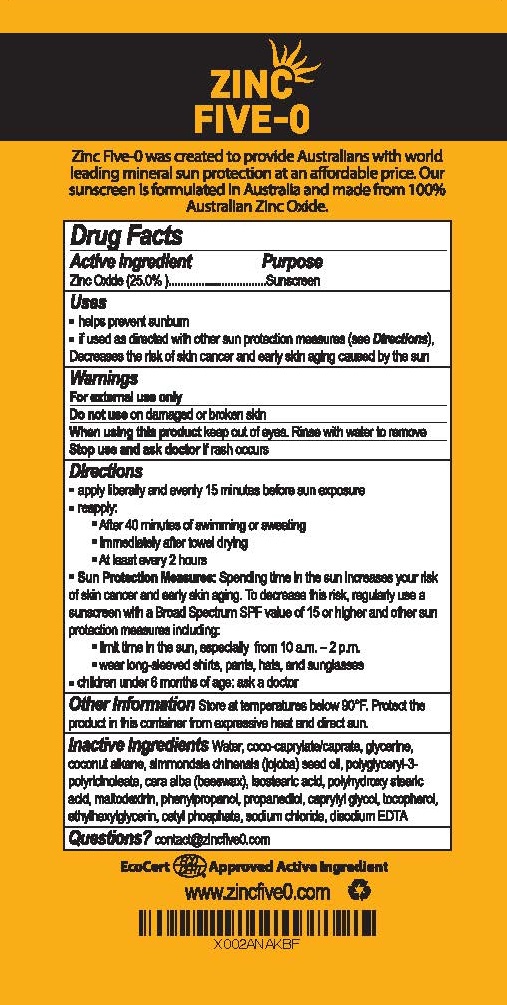 DRUG LABEL: ZINC FIVE-O
NDC: 80982-003 | Form: LOTION
Manufacturer: ASTIVITA LIMITED
Category: otc | Type: HUMAN OTC DRUG LABEL
Date: 20220127

ACTIVE INGREDIENTS: ZINC OXIDE 25 g/240 g
INACTIVE INGREDIENTS: WATER; COCO-CAPRYLATE/CAPRATE; GLYCERIN; COCONUT ALKANES; JOJOBA OIL; POLYGLYCERYL-3 RICINOLEATE; YELLOW WAX; ISOSTEARIC ACID; POLYHYDROXYSTEARIC ACID (2300 MW); MALTODEXTRIN; PHENYLPROPANOL; PROPANEDIOL; CAPRYLYL GLYCOL; TOCOPHEROL; ETHYLHEXYLGLYCERIN; CETYL PHOSPHATE; SODIUM CHLORIDE; EDETATE DISODIUM

ZINC FIVE-O SPF-50

ACTIVE INGREDIENT

ZINC OXIDE 25%

PURPOSE

SUNSCREEN

USES

- Helps prevent sunburn
- If used as directed with other sun protection measures (see Directions), decreased the risk of skin cancer and early skin aging caused by the sun

WARNINGS

For external use only
Do not use on damaged or broken skin.
When using this product keep out of eyes. Rinse with water to remove.
Stop use and ask doctor if rash occurs.

DIRECTIONS:

Apply liberally and evenly 15 minutes before sun exposure.

Reapply: • After 40 minutes of swimming or sweating • Immediately after towel drying • At least every 2 hours Sun Protection Measures: • Spending time in the sun increases your risk of skin cancer and early skin aging • To decrease this risk, regularly use a sunscreen with a Broad Spectrum SPF value of 15 or higher and other sun protection measures including:
•Limit time in the sun, especially from 10 a.m. – 2 p.m.
•Wear long-sleeved shirts, pants, hats, and sunglasses
•Children under 6 months of age: ask a doctor.

OTHER INFORMATION

Store at temperatures below 90°F.

INACTIVE INGREDIENTS

Coco-caprylate/caprate, glycerine, coconut alkane, simmondsia chinensis (jojoba) seed oil, polyglyceryl-3-polyricinoleate, cera alba (beeswax), isostearic acid, polyhydroxy stearic acid, maltodextrin, phenylpropanol, propanediol, caprylyl glycol, tocopherol, ethylhexylglycerin, cetyl phosphate, sodium chloride, disodium EDTA